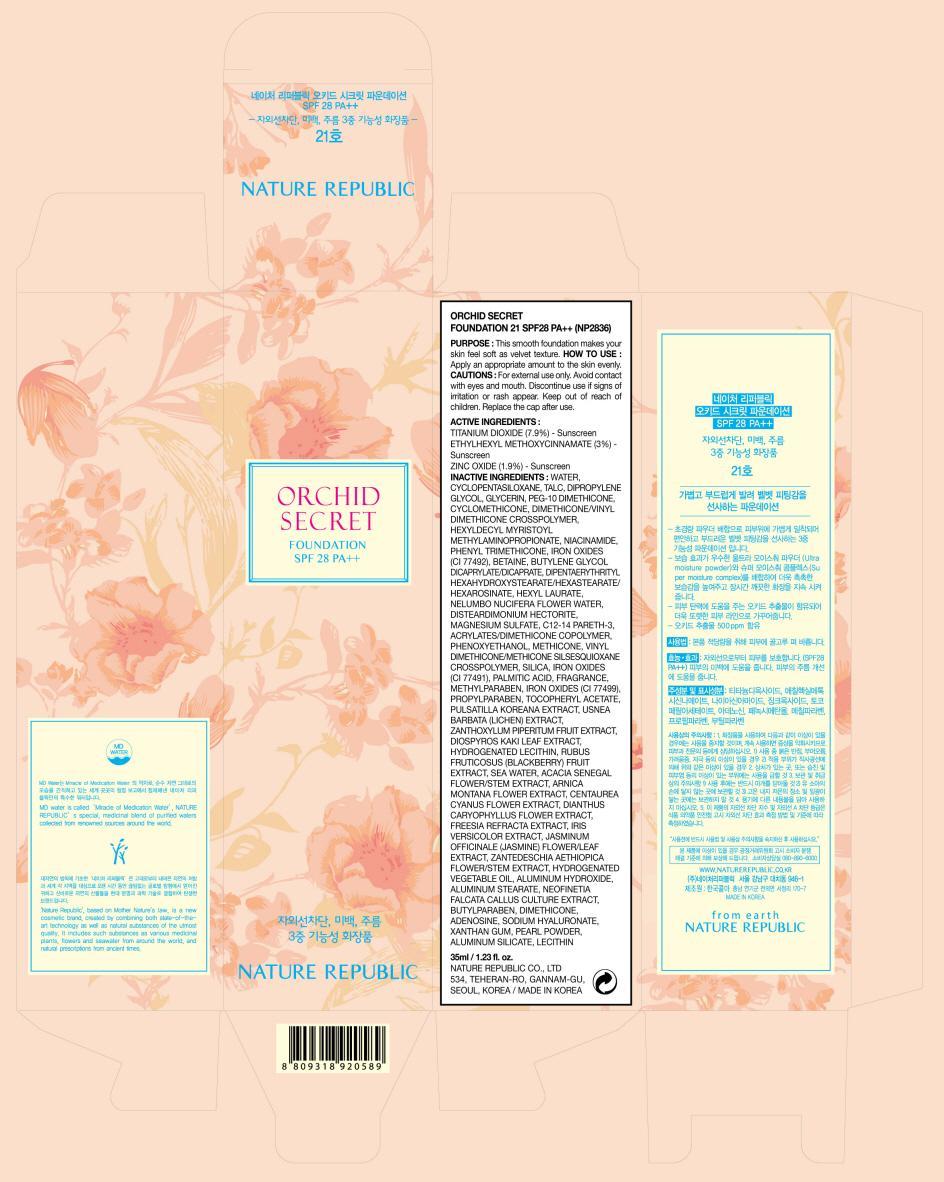 DRUG LABEL: ORCHID SECRET FOUNDATION
NDC: 51346-032 | Form: CREAM
Manufacturer: NATURE REPUBLIC CO., LTD.
Category: otc | Type: HUMAN OTC DRUG LABEL
Date: 20120827

ACTIVE INGREDIENTS: TITANIUM DIOXIDE 2.76 g/35 mL; OCTINOXATE 1.05 g/35 mL; ZINC OXIDE 0.66 g/35 mL
INACTIVE INGREDIENTS: WATER; CYCLOMETHICONE 5; TALC; DIPROPYLENE GLYCOL; GLYCERIN

ACTIVE INGREDIENT

Active Ingredients: TITANIUM DIOXIDE 7.9%, ETHYLHEXYL METHOXYCINNAMATE 3%, ZINC OXIDE 1.9%

INACTIVE INGREDIENT

Inactive Ingredients:
WATER, CYCLOPENTASILOXANE, TALC, DIPROPYLENE GLYCOL, GLYCERIN, PEG-10 DIMETHICONE, CYCLOMETHICONE, DIMETHICONE/VINYL DIMETHICONE CROSSPOLYMER, HEXYLDECYL MYRISTOYL METHYLAMINOPROPIONATE, NIACINAMIDE, PHENYL TRIMETHICONE, IRON OXIDES, BETAINE, BUTYLENE GLYCOL DICAPRYLATE/DICAPRATE, DIPENTAERYTHRITYL HEXAHYDROXYSTEARATE/HEXASTEARATE/HEXAROSINATE, HEXYL LAURATE, NELUMBO NUCIFERA FLOWER WATER, DISTEARDIMONIUM HECTORITE, MAGNESIUM SULFATE, C12-14 PARETH-3, ACRYLATES/DIMETHICONE COPOLYMER, PHENOXYETHANOL, METHICONE, VINYL DIMETHICONE/METHICONE SILSESQUIOXANE CROSSPOLYMER, SILICA, PALMITIC ACID, FRAGRANCE, METHYLPARABEN, PROPYLPARABEN, TOCOPHERYL ACETATE, PULSATILLA KOREANA EXTRACT, USNEA BARBATA (LICHEN) EXTRACT, ZANTHOXYLUM PIPERITUM FRUIT EXTRACT, DIOSPYROS KAKI LEAF EXTRACT, HYDROGENATED LECITHIN, RUBUS FRUTICOSUS (BLACKBERRY) FRUIT EXTRACT, SEA WATER, ACACIA SENEGAL FLOWER/STEM EXTRACT, ARNICA MONTANA FLOWER EXTRACT, CENTAUREA CYANUS FLOWER EXTRACT, DIANTHUS CARYOPHYLLUS FLOWER EXTRACT, FREESIA REFRACTA EXTRACT, IRIS VERSICOLOR EXTRACT, JASMINUM OFFICINALE (JASMINE) FLOWER/LEAF EXTRACT, ZANTEDESCHIA AETHIOPICA FLOWER/STEM EXTRACT,
HYDROGENATED VEGETABLE OIL, ALUMINUM HYDROXIDE, ALUMINUM STEARATE, NEOFINETIA FALCATA CALLUS CULTURE EXTRACT, BUTYLPARABEN, ADENOSINE, SODIUM HYALURONATE, XANTHAN GUM, PEARL POWDER, ALUMINUM SILICATE, LECITHIN

PURPOSE

Purpose: This smooth foundation makes your skin feel soft as velvet texture.

WARNINGS

Cautions:
For external use only.
Avoid contact with eyes and mouth.
Discontinue use if signs of irritation or rash appear.
Keep out of reach of children.
Replace the cap after use.

KEEP OUT OF REACH OF CHILDREN

INDICATIONS AND USAGE

How to Use: Apply an appropriate amount to the skin evenly.

DOSAGE AND ADMINISTRATION

How to Use: Apply an appropriate amount to the skin evenly.